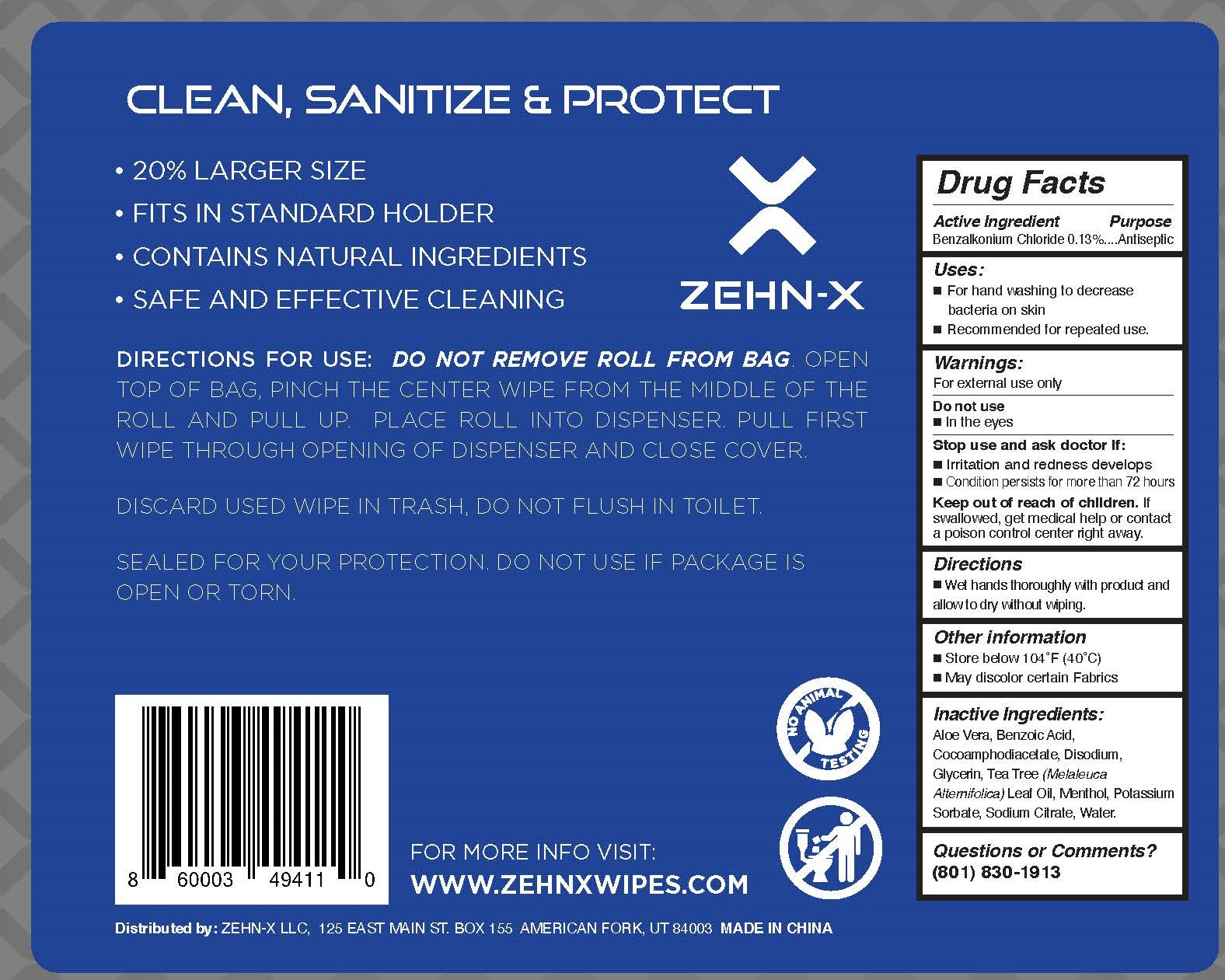 DRUG LABEL: ZEHN-X  ANTISEPTIC SANITIZING WIPES
NDC: 75714-001 | Form: SWAB
Manufacturer: HANGZHOU CLEAN NONWOVEN CO.,LTD
Category: otc | Type: HUMAN OTC DRUG LABEL
Date: 20210708

ACTIVE INGREDIENTS: BENZALKONIUM CHLORIDE 0.13 g/100 g
INACTIVE INGREDIENTS: WATER; ALOE VERA LEAF; TEA TREE OIL; MENTHOL; POTASSIUM SORBATE; SODIUM CITRATE; DISODIUM COCOAMPHODIACETATE; GLYCERIN; BENZOIC ACID

75714-001 ANTISEPTIC SANITIZING WIPES

Active Ingredient

Benzalkonium Chloride 0.13%

Purpose

Antiseptic

USE

■For hand washing to decrease
bacteria on skin
■Recommended for repeated use.

Warning

For external use only
Do not use
■In the eyes
Stop use and ask doctor If:
■Irritation and redness develops
■Condition persists for more than 72 hours

Keep out of reach of children. If
swallowed, get medical help or contact
a poison control center right away.

Directions

■Wet hands thoroughly with product and
allowto dry without wiping.

Inactive ingredients

Aloe Vera, Benzoic Acid,
Cocoamphodiacetate, Disodium,
Glycerin, Tea Tree (Melaleuca
Atemifolica) Leaf Oil, Menthol, Potassium
Sorbate, Sodium Citrate, Water.